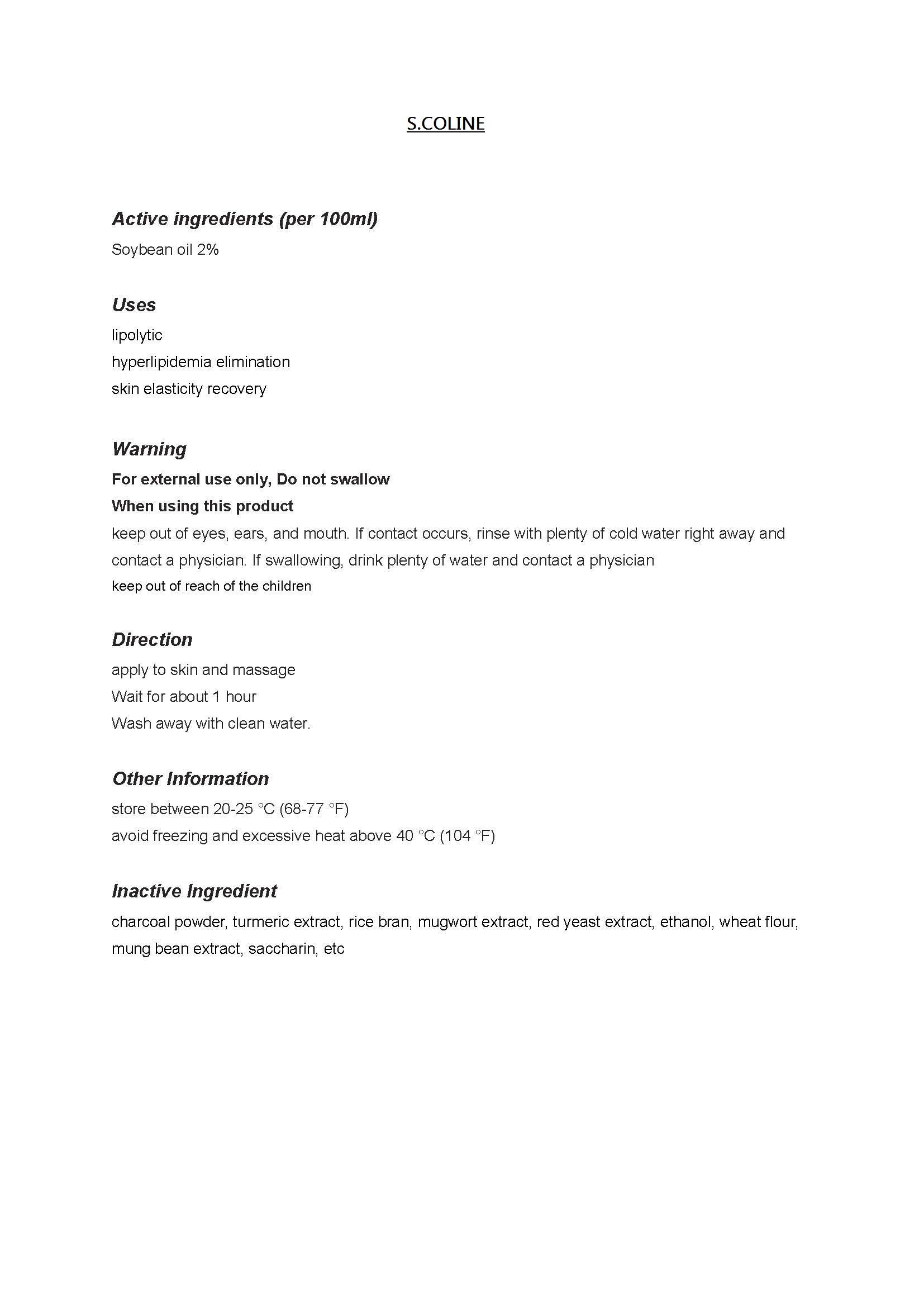 DRUG LABEL: S.COLINE
NDC: 61164-6001 | Form: LIQUID
Manufacturer: Barona Co., Ltd 
Category: otc | Type: HUMAN OTC DRUG LABEL
Date: 20150205

ACTIVE INGREDIENTS: HYDROGENATED SOYBEAN OIL 2 g/100 mL
INACTIVE INGREDIENTS: ARTEMISIA PRINCEPS LEAF; CITRUS MAXIMA FRUIT OIL; MUNG BEAN

Drug Facts

ACTIVE INGREDIENT

soybean oil

INACTIVE INGREDIENT

charcoal powder, turmeric extract, rice bran, mugwort extract, red yeast extract, ethanol, wheat flour, mung bean extract, saccharin, etc

PURPOSE

lipolytic
hyperlipidemia elimination
skin elasticity recovery

keep out of reach of the children

INDICATIONS AND USAGE

apply to skin and massage
Wait for about 1 hour
Wash away with clean water.

WARNINGS

do not swallow
do not use if you have skin wounds
do not use if you have allergies

DOSAGE AND ADMINISTRATION

for topical use only